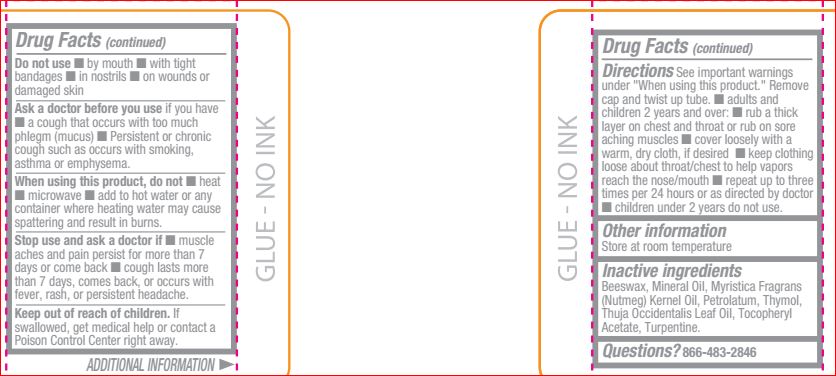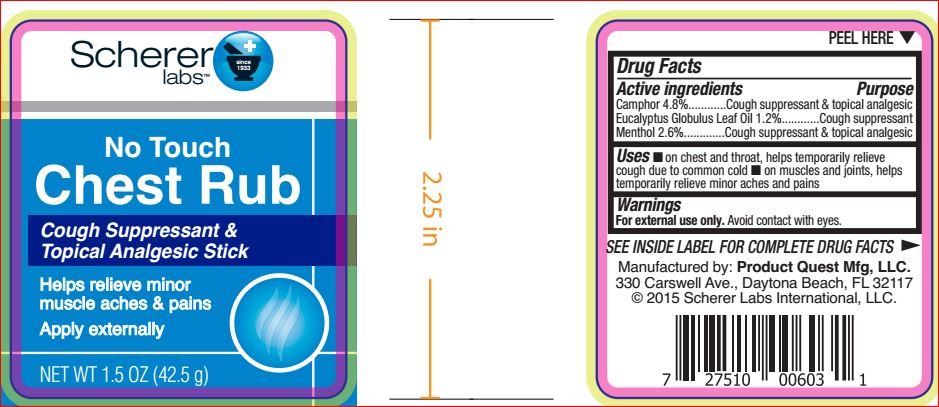 DRUG LABEL: No Touch  Chest Rub
NDC: 64048-5116 | Form: STICK
Manufacturer: Product Quest Mfg.
Category: otc | Type: HUMAN OTC DRUG LABEL
Date: 20180807

ACTIVE INGREDIENTS: CAMPHOR (SYNTHETIC) 4.8 g/100 g; EUCALYPTUS OIL 1.2 g/100 g; Menthol 2.6 g/100 g
INACTIVE INGREDIENTS: YELLOW WAX; Mineral Oil; NUTMEG OIL; Petrolatum; Thymol; CEDAR LEAF OIL; .ALPHA.-TOCOPHEROL ACETATE; Turpentine

Drug Facts

Active ingredients Purpose

Camphor 4.8%..........................................Cough suppressant & topical analgesic
Eucalyptus Globulus Leaf Oil 1.2%.........Cough suppressant
Menthol 2.6%............................................Cough suppressant & topical analgesic

Directions

See important warnings under "When using this product." Remove cap and twist up tube.

■ adults and children 2 years and over: ■ rub a thick layer on chest and throat or rub on sore aching muscles ■ cover loosely with a warm, dry cloth, if desired ■ keep clothing loose about throat/chest to help vapors reach the nose/mouth ■ repeat up to three times per 24 hours or as directed by doctor ■ children under 2 years do not use.

Warnings For external use only

Avoid contact with eyes.

Do not use ■ by mouth ■ with tight
bandages ■ in nostrils ■ on wounds or
damaged skin
Ask a doctor before you use if you have
■ a cough that occurs with too much
phlegm (mucus) ■ Persistent or chronic
cough such as occurs with smoking,
asthma or emphysema.
When using this product, do not ■ heat
■ microwave ■ add to hot water or any
container where heating water may cause
spattering and result in burns.
Stop use and ask a doctor if ■ muscle
aches and pain persist for more than 7
days or come back ■ cough lasts more
than 7 days, comes back, or occurs with
fever, rash, or persistent headache

Keep out of reach of children.

If swallowed, get medical help or contact a Poison Control Center right away

Uses

■ on chest and throat, helps temporarily relieve cough due to common cold ■ on muscles and joints, helps temporarily relieve minor aches and pains

Inactive ingredients

Beeswax
Mineral Oil
Myristica Fragrans (Nutmeg) Kernel Oil
Petrolatum
Thymol
Thuja Occidentalis Leaf Oil
Tocopheryl Acetate
Turpentine